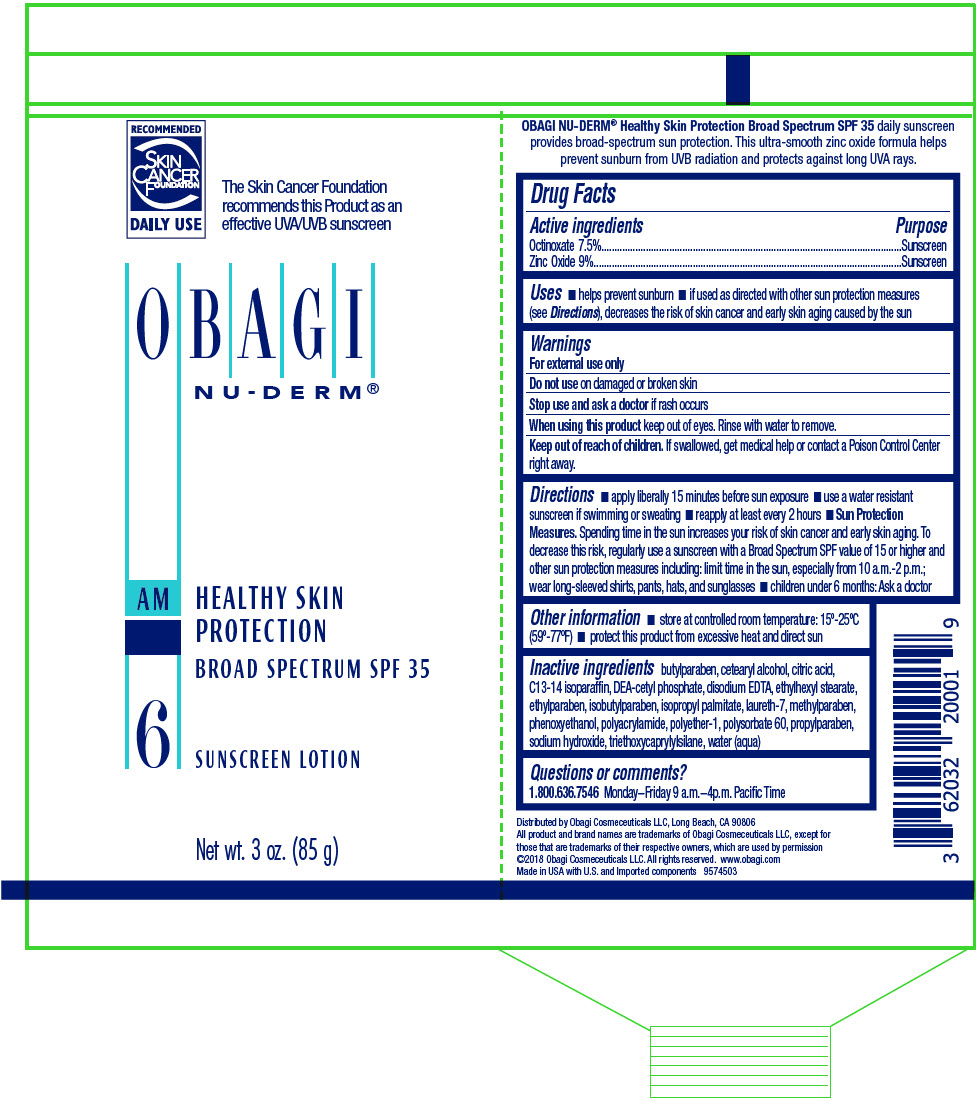 DRUG LABEL: NU-DERM HEALTHY SKIN PROTECTION
NDC: 62032-200 | Form: CREAM
Manufacturer: Obagi Cosmeceuticals LLC
Category: otc | Type: HUMAN OTC DRUG LABEL
Date: 20250101

ACTIVE INGREDIENTS: OCTINOXATE 75 mg/1 mL; ZINC OXIDE 90 mg/1 mL
INACTIVE INGREDIENTS: ISOPROPYL PALMITATE; WATER; ETHYLHEXYL STEARATE; CETOSTEARYL ALCOHOL; POLYSORBATE 60; C13-14 ISOPARAFFIN; METHYLPARABEN; LAURETH-7; PROPYLPARABEN; EDETATE DISODIUM; BUTYLPARABEN; DIETHANOLAMINE CETYL PHOSPHATE; PHENOXYETHANOL; ETHYLPARABEN; ISOBUTYLPARABEN; SODIUM HYDROXIDE; TRIETHOXYCAPRYLYLSILANE; CITRIC ACID MONOHYDRATE

NU-DERM
HEALTHY SKIN
PROTECTION
SPF 35

Drug Facts

ACTIVE INGREDIENT

Active ingredients | Purpose
Octinoxate 7.5% | Sunscreen
Zinc Oxide 9% | Sunscreen

Uses

- helps prevent sunburn
- if used as directed with other sun protection measures (see Directions), decreases the risk of skin cancer and early skin aging caused by the sun

Warnings

For external use only

Do not use on damaged or broken skin

Stop use and ask a doctor if rash occurs

When using this product keep out of eyes. Rinse with water to remove.

Keep out of reach of children. If swallowed, get medical help or contact a Poison Control Center right away.

Directions

- apply liberally 15 minutes before sun exposure
- use a water resistant sunscreen if swimming or sweating
- reapply at least every 2 hours
- Sun Protection Measures. Spending time in the sun increases your risk of skin cancer and early skin aging. To decrease this risk, regularly use a sunscreen with a Broad Spectrum SPF value of 15 or higher and other sun protection measures including: limit time in the sun, especially from 10 a.m.-2 p.m.; wear long-sleeved shirts, pants, hats, and sunglasses
- children under 6 months: Ask a doctor

Other information

- store at controlled room temperature: 15°-25°C (59°-77°F)
- protect this product from excessive heat and direct sun

Inactive ingredients

butylparaben, cetearyl alcohol, citric acid, C13-14 isoparaffin, DEA-cetyl phosphate, disodium EDTA, ethylhexyl stearate, ethylparaben, isobutylparaben, isopropyl palmitate, laureth-7, methylparaben, phenoxyethanol, polyacrylamide, polyether-1, polysorbate 60, propylparaben, sodium hydroxide, triethoxycaprylylsilane, water (aqua)

Questions or comments?

1.800.636.7546 Monday−Friday 9 a.m.−4p.m. Pacific Time

Distributed by Obagi Cosmeceuticals LLC, Long Beach, CA 90806

PRINCIPAL DISPLAY PANEL - 85 g Bottle Label

RECOMMENDED
SKIN
CANCER
FOUNDATION
DAILY USE

The Skin Cancer Foundation
recommends this Product as an
effective UVA/UVB sunscreen

OBAGI
NU-DERM®

AM
HEALTHY SKIN
PROTECTION

BROAD SPECTRUM SPF 35

6
SUNSCREEN LOTION

Net wt. 3 oz. (85 g)